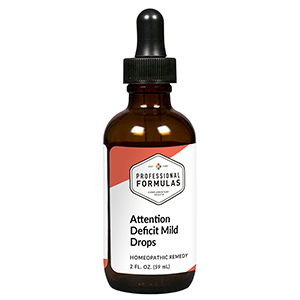 DRUG LABEL: Attention Deficit Mild Drops
NDC: 63083-2146 | Form: LIQUID
Manufacturer: Professional Complementary Health Formulas
Category: homeopathic | Type: HUMAN OTC DRUG LABEL
Date: 20190815

ACTIVE INGREDIENTS: .GAMMA.-AMINOBUTYRIC ACID 3 [hp_X]/59 mL; GINKGO 3 [hp_X]/59 mL; BOS TAURUS BRAIN 6 [hp_X]/59 mL; BOS TAURUS HYPOTHALAMUS 6 [hp_X]/59 mL; BEEF KIDNEY 6 [hp_X]/59 mL; BEEF LIVER 6 [hp_X]/59 mL; BOS TAURUS PANCREAS 6 [hp_X]/59 mL; SUS SCROFA PINEAL GLAND 6 [hp_X]/59 mL; SILVER NITRATE 30 [hp_X]/59 mL; AMARYLLIS BELLADONNA WHOLE 30 [hp_X]/59 mL; COFFEA ARABICA SEED, ROASTED 30 [hp_X]/59 mL; PHOSPHORUS 30 [hp_X]/59 mL; AMBERGRIS 30 [hp_X]/59 mL; BARIUM CARBONATE 30 [hp_X]/59 mL; BARIUM CHLORIDE DIHYDRATE 30 [hp_X]/59 mL; INSULIN GLULISINE 30 [hp_X]/59 mL; LYCOPODIUM CLAVATUM SPORE 30 [hp_X]/59 mL; GONORRHEAL URETHRAL SECRETION HUMAN 30 [hp_X]/59 mL; DATURA STRAMONIUM 30 [hp_X]/59 mL; THUJA OCCIDENTALIS LEAF 30 [hp_X]/59 mL; BOVINE TUBERCULIN 30 [hp_X]/59 mL; VERATRUM ALBUM ROOT 30 [hp_X]/59 mL
INACTIVE INGREDIENTS: ALCOHOL; WATER

C146

ACTIVE INGREDIENTS

GABA 3X
Ginkgo biloba 3X
Brain 6X
Hypothalamus 6X
Kidney 6X
Liver 6X
Pancreas 6X
Pineal 6X
Argentum nitricum 30X
Belladonna 30X
Coffea tosta 30X
Phosphorus 30X
Ambra grisea 30X, 60X
Baryta carbonica 30X, 60X
Baryta muriatica 30X, 60X
DNA insulin 30X, 60X
Lycopodium clavatum 30X
Medorrhinum 30X, 60X
Stramonium 30X, 60X
Thuja occidentalis 30X, 60X
Tuberculinum 30X, 60X
Veratrum album 30X, 60X

QUESTIONS

Professional Formulas

PO Box 2034 Lake Oswego, OR 97035

INDICATIONS

For the temporary relief of mild excitability, fidgeting, or lack of restraint or focus.*

PURPOSE

*Claims based on traditional homeopathic practice, not accepted medical evidence. Not FDA evaluated.

WARNINGS

In case of overdose, get medical help or contact a poison control center right away.

Keep out of the reach of children.

PREGNANCY OR BREAST FEEDING

If pregnant or breastfeeding, ask a healthcare professional before use.

DIRECTIONS

Place drops under tongue 30 minutes before/after meals. Adults and children 12 years and over: Take 10 drops up to 3 times per day. Consult a physician for use in children under 12 years of age.

OTHER INFORMATION

Tamper resistant. If seal is broken, do not use. After opening, close container tightly and store at room temperature away from heat.

INACTIVE INGREDIENTS

10% ethanol, purified water, 8% vegetable glycerin (from soy).

LABEL

Est 1985

Professional Formulas

Complementary Health

Attention Deficit Mild Drops

Homeopathic Remedy

2 FL. OZ. (59 mL)